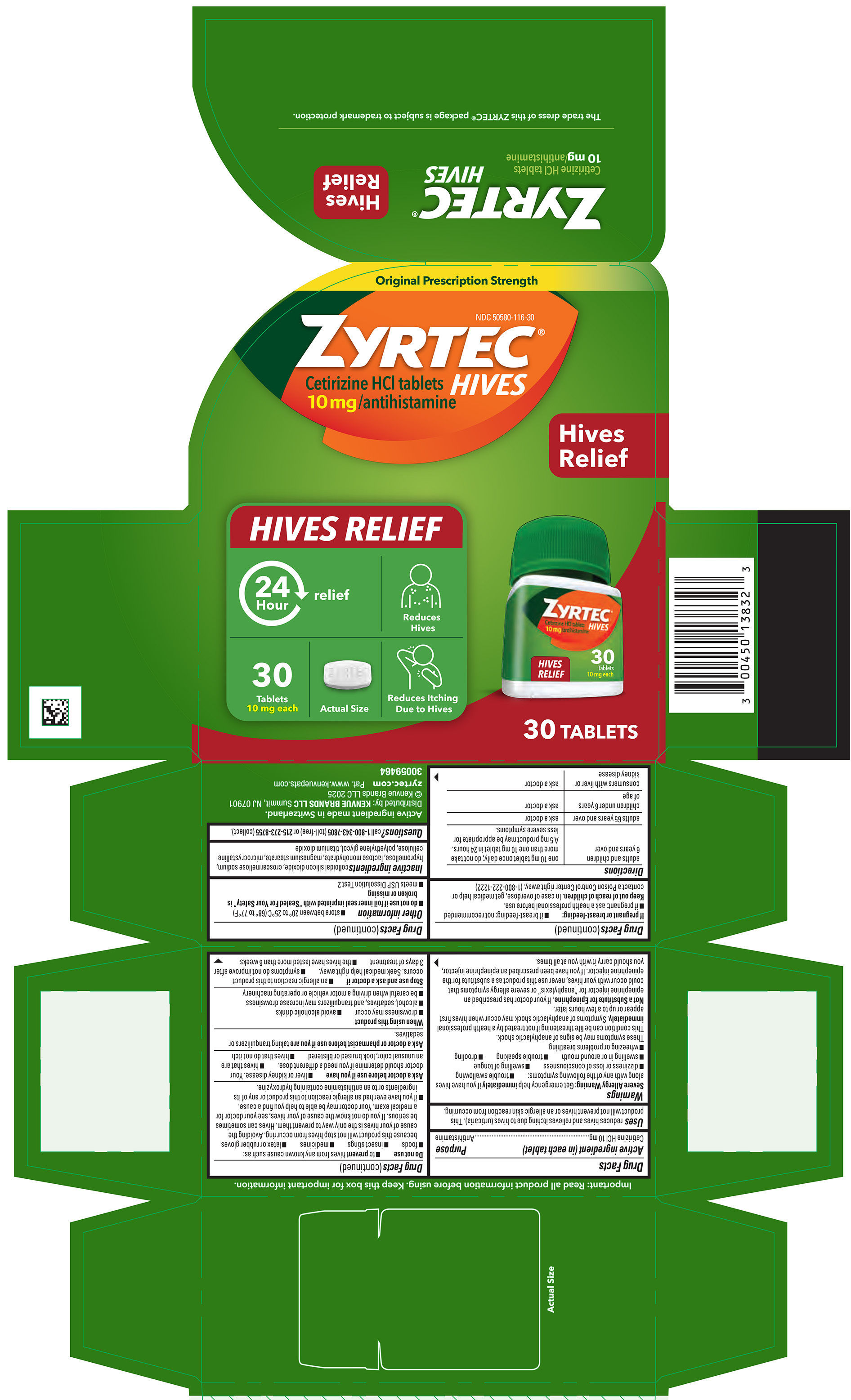 DRUG LABEL: ZYRTEC Hives
NDC: 50580-116 | Form: TABLET, FILM COATED
Manufacturer: Kenvue Brands LLC
Category: otc | Type: HUMAN OTC DRUG LABEL
Date: 20250616

ACTIVE INGREDIENTS: CETIRIZINE HYDROCHLORIDE 10 mg/1 1
INACTIVE INGREDIENTS: HYPROMELLOSES; LACTOSE MONOHYDRATE; SILICON DIOXIDE; MAGNESIUM STEARATE; MICROCRYSTALLINE CELLULOSE; CROSCARMELLOSE SODIUM; POLYETHYLENE GLYCOL, UNSPECIFIED; TITANIUM DIOXIDE

ZYRTEC Hives

Drug Facts

Active ingredient (in each tablet)

Cetirizine HCl 10 mg

Purpose

Antihistamine

Uses

reduces hives and relieves itching due to hives (urticaria). This product will not prevent hives or an allergic skin reaction from occurring.

Warnings

Severe Allergy Warning: Get emergency help immediately if you have hives along with any of the following symptoms:

- trouble swallowing
- dizziness or loss of consciousness
- swelling of tongue
- swelling in or around mouth
- trouble speaking
- drooling
- wheezing or problems breathing

These symptoms may be signs of anaphylactic shock.
This condition can be life threatening if not treated by a health professional immediately. Symptoms of anaphylactic shock may occur when hives first appear or up to a few hours later.

Not a Substitute for Epinephrine. If your doctor has prescribed an epinephrine injector for "anaphylaxis" or severe allergy symptoms that could occur with your hives, never use this product as a substitute for the epinephrine injector. If you have been prescribed an epinephrine injector, you should carry it with you at all times.

Do not use

- to prevent hives from any known cause such as:

-foods

-insect stings

-medicines

-latex or rubber gloves

because this product will not stop hives from occurring. Avoiding the cause of your hives is the only way to prevent them. Hives can sometimes be serious. If you do not know the cause of your hives, see your doctor for a medical exam. Your doctor may be able to help you find a cause.

- if you have ever had an allergic reaction to this product or any of its ingredients or to an antihistamine containing hydroxyzine.

Ask a doctor before use if you have

- liver or kidney disease. Your doctor should determine if you need a different dose.
- hives that are an unusual color, look bruised or blistered
- hives that do not itch

Ask a doctor or pharmacist before use if you are taking tranquilizers or sedatives.

When using this product

- drowsiness may occur
- avoid alcoholic drinks
- alcohol, sedatives, and tranquilizers may increase drowsiness
- be careful when driving a motor vehicle or operating machinery

Stop use and ask a doctor if

- an allergic reaction to this product occurs. Seek medical help right away.
- symptoms do not improve after 3 days of treatment
- the hives have lasted more than 6 weeks

If pregnant or breast-feeding:

- If breast-feeding: not recommended
- if pregnant: ask a health professional before use.

Keep out of reach of children. In case of overdose , get medical help or contact a Poison Control Center right away. (1-800-222-1222)

Directions

adults and children 6 years and over | one 10 mg tablet once daily; do not take more than one 10 mg tablet in 24 hours. A 5 mg product may be appropriate for less severe symptoms.
adults 65 years and over | ask a doctor
children under 6 years of age | ask a doctor
consumers with liver or kidney disease | ask a doctor

Other information

- store between 20° to 25°C (68° to 77°F)
- do not use if foil inner seal imprinted with “Sealed For Your Safety” is broken or missing
- meets USP Dissolution Test 2

Inactive ingredients

colloidal silicon dioxide, croscarmellose sodium,hypromellose, lactose monohydrate, magnesium stearate, microcrystalline cellulose, polyethylene glycol, titanium dioxide

QUESTIONS

Questions? call 1-800-343-7805 (toll-free) or 215-273-8755 (collect).

PACKAGE LABEL

Original Prescription Strength

NDC 50580-116-30

ZYRTEC® HIVES
Cetirizine HCl tablets
10mg/antihistamine

Hives Relief

24 Hour relief

Reduces Hives

Reduces Itching Due to Hives

30 Tablets 10 mg each

Actual Size

30 TABLETS